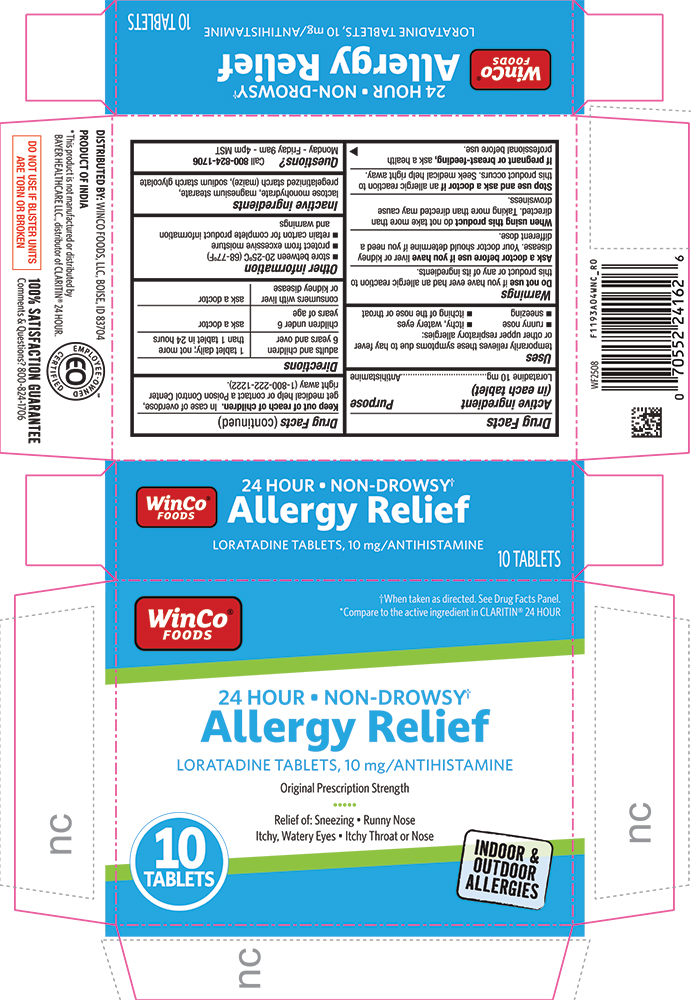 DRUG LABEL: Allergy Relief
NDC: 67091-493 | Form: TABLET
Manufacturer: WinCo Foods, LLC
Category: otc | Type: HUMAN OTC DRUG LABEL
Date: 20251103

ACTIVE INGREDIENTS: LORATADINE 10 mg/1 1
INACTIVE INGREDIENTS: LACTOSE MONOHYDRATE; MAGNESIUM STEARATE; STARCH, CORN; SODIUM STARCH GLYCOLATE TYPE A POTATO

1193A-WNC-2025-1103

Drug Facts

Active ingredient (in each tablet)

Loratadine 10 mg

Purpose

Antihistamine

Uses

temporarily relieves these symptoms due to hay fever or other upper respiratory allergies:

- runny nose
- sneezing
- itchy, watery eyes
- itching of the nose or throat

Warnings

DO NOT USE

Do not useif you have ever had an allergic reaction to this product or any of its ingredients.

Ask a doctor before use if you haveliver or kidney disease. Your doctor should determine if you need a different dose.

WHEN USING

When using this productdo not take more than directed. Taking more than directed may cause drowsiness.

Stop use and ask a doctor if an allergic reaction to this product occurs. Seek medical help right away.

PREGNANCY OR BREAST FEEDING

If pregnant or breast-feeding, ask a health professional before use

Keep out of reach of children.

In case of overdose, get medical help or contact a Poison Control Center right away (1-800-222-1222).

Directions

adults and children 6 years and over | 1 tablet daily; not more than 1 tablet in 24 hours
children under 6 years of age | ask a doctor
consumers with liver or kidney disease | ask a doctor

Other information

- store between 20 to 25°C (68 to 77°F)
- retain carton for complete product information and warnings

Inactive ingredients

lactose monohydrate, magnesium stearate, pregelatinized starch (maize), sodium starch glycolate

Questions?

Call 800-824-1706Monday - Friday 9am - 4pm MST

PRINCIPAL DISPLAY PANEL

WinCo® Foods

†When taken as directed. See Drug Facts Panel.

*Compare to the active ingredient in CLARITIN® 24 HOUR

24 HOUR • NON-DROWSY†

Allergy Relief

LORATADINE TABLETS, 10 MG/ANTIHISTAMINE

Original Prescription Strength

Relief of: Sneezing • Runny Nose

Itchy, Watery Eyes • Itchy Throar or Nose

10 TABLETS

INDOOR & OUDOOR ALLERGIES